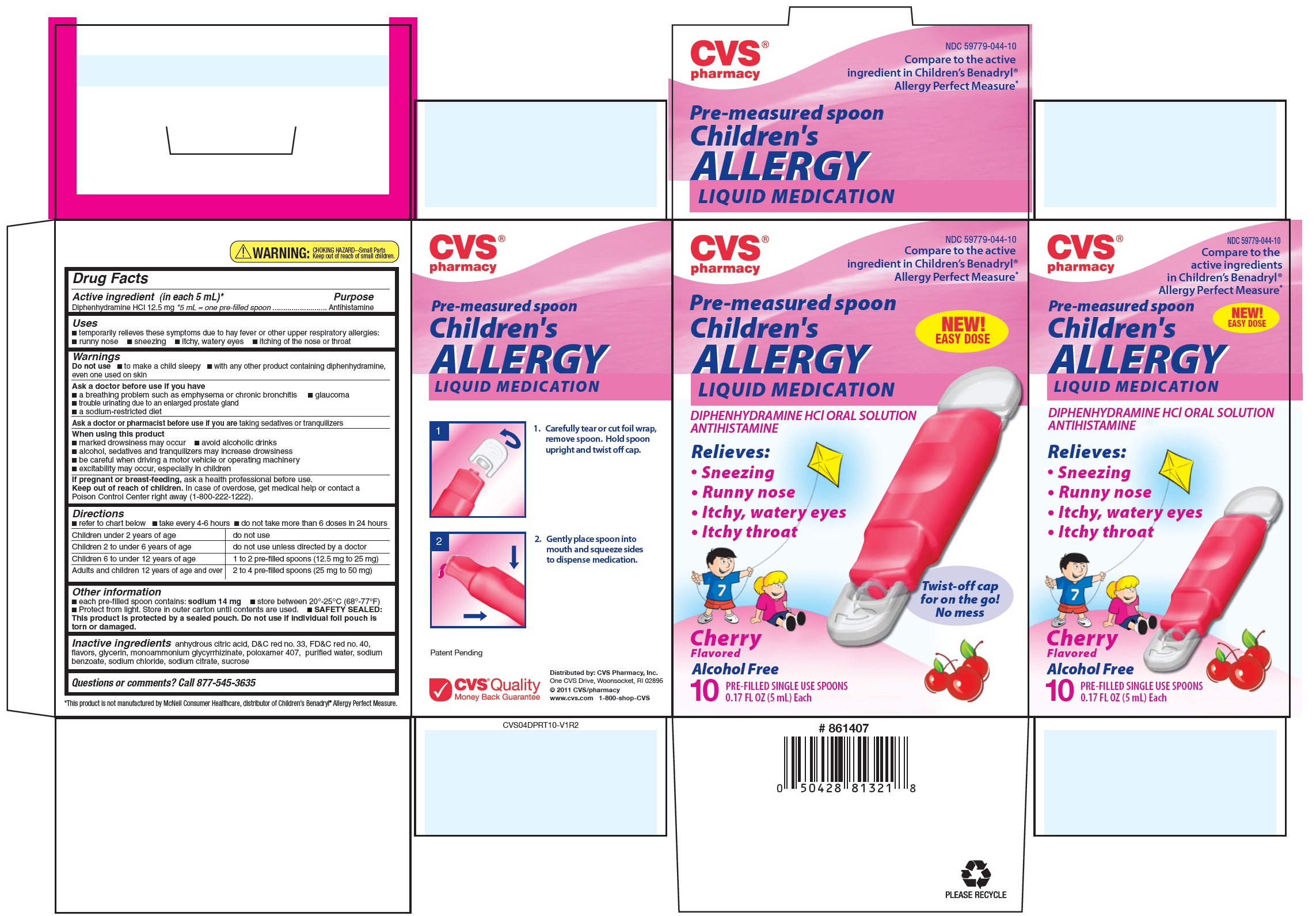 DRUG LABEL: CVS Pharmacy Pre-measured spoon Childrens
NDC: 59779-044 | Form: LIQUID
Manufacturer: CVS PHARMACY, INC.
Category: otc | Type: HUMAN OTC DRUG LABEL
Date: 20110823

ACTIVE INGREDIENTS: Diphenhydramine Hydrochloride 12.5 mg/5 mL
INACTIVE INGREDIENTS: anhydrous citric acid; D&C red NO. 33; FD&C red NO. 40; glycerin; ammonium glycyrrhizate; poloxamer 407; water; sodium benzoate; sodium chloride; sodium citrate; sucrose

Drug Facts

Active ingredient (in each 5 mL)*

Diphenhydramine HCl 12.5 mg

*5 mL = one pre-filled spoon

Purpose

Antihistamine

Uses

- temporarily relieves these symptoms due to hay fever or other upper respiratory allergies:
  - runny nose
  - sneezing
  - itchy, watery eyes
  - itching of the nose or throat

Warnings

Do not use

- to make a child sleepy
- with any other product containing diphenhydramine, even one used on skin

Ask a doctor before use if you have

- a breathing problem such as emphysema or chronic bronchitis
- glaucoma
- trouble urinating due to an enlarged prostate gland
- a sodium-restricted diet

Ask a doctor or pharmacist before use if you are taking sedatives or tranquilizers

When using this product

- marked drowsiness may occur
- avoid alcoholic drinks
- alcohol, sedatives and tranquilizers may increase drowsiness
- be careful when driving a motor vehicle or operating machinery
- excitability may occur, especially in children

PREGNANCY OR BREAST FEEDING

If pregnant or breast-feeding, ask a health professional before use.

Keep out of reach of children. In case of overdose, get medical help or contact a Poison Control Center right away (1-800-222-1222).

Directions

- refer to chart below
- take every 4 to 6 hours
- do not take more than 6 doses in 24 hours

Children under 2 years of age | do not use
Children 2 to 5 years of age | do not use unless directed by a doctor
Children 6 to 11 years of age | 1 to 2 pre-filled spoons (12.5 mg to 25 mg)
Adults and children 12 years of age and over | 2 to 4 pre-filled spoons (25 mg to 50 mg)

Other information

- each pre-filled spoon contains: sodium 14 mg
- store between 20-25°C (68-77°F).
- Protect from light. Store in outer carton until contents used.
- SAFETY SEALED: This product is protected by a sealed pouch. Do not use if individual foil pouch is torn or damaged

Inactive ingredients

anhydrous citric acid, D&C red #33, FD&C red #40, flavors, glycerin, monoammonium glycyrrhizinate, poloxamer 407, purified water, sodium benzoate, sodium chloride, sodium citrate, sucrose

Questions or comments?

Call 877-545-3635

*This product is not manufactured or distributed by McNeil Consumer Healthcare, distributor of Children's Benadryl® Allergy Perfect Measure

PRINCIPAL DISPLAY PANEL

NDC 59779-044-10

CVS Pharmacy Pre-measured spoon
Children's
ALLERGY LIQUID MEDICATION®

Diphenhydramine HCI
Oral Solution Antihistamine

Relieves:

- Sneezing
- Runny Nose
- Itchy, watery eyes
- Itchy Throat

Cherry Flavored

Alcohol Free

10 PRE-FILLED SINGLE USE SPOONS**
0.17 FL OZ (5 mL) EACH